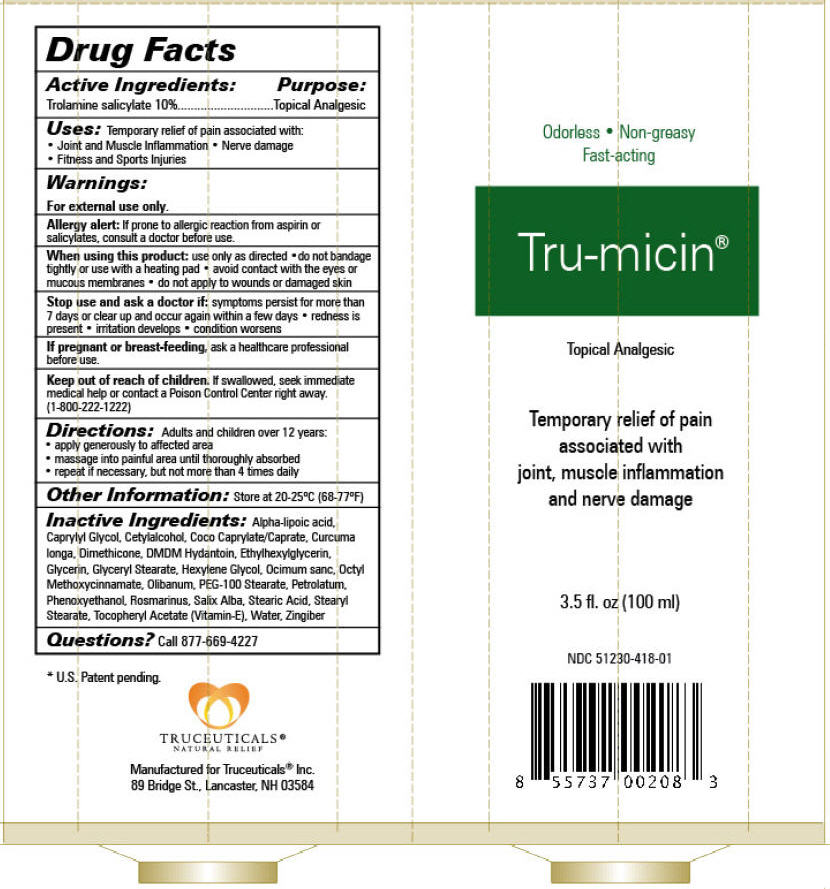 DRUG LABEL: Tru-micin
NDC: 51230-418 | Form: LOTION
Manufacturer: Truceuticals, LLC
Category: otc | Type: HUMAN OTC DRUG LABEL
Date: 20130605

ACTIVE INGREDIENTS: Trolamine 0.1 mg/1 mL
INACTIVE INGREDIENTS: Glycerin; Coco-Caprylate; Glyceryl Monostearate; PEG-100 Stearate; Octinoxate; Stearic Acid; Cetyl Alcohol; Stearyl Stearate; Dimethicone; Petrolatum; .Alpha.-Tocopherol Acetate; Phenoxyethanol; Caprylyl Glycol; Ethylhexylglycerin; Hexylene Glycol; DMDM Hydantoin; Water; Turmeric; INDIAN FRANKINCENSE; .Alpha.-Lipoic Acid; Salix Alba Bark; Ocimum Tenuiflorum Top; Ginger; Rosemary

Tru-micin®

Drug Facts

Active Ingredients

Trolamine salicylate 10%

Purpose

Topical Analgesic

Uses

Temporary relief of pain associated with:

- Joint and Muscle Inflammation
- Nerve damage
- Fitness and Sports Injuries

Warnings

For external use only.

Allergy alert

If prone to allergic reaction from aspirin or salicylates, consult a doctor before use.

When using this product

use only as directed

- do not bandage tightly or use with a heating pad
- avoid contact with the eyes or mucous membranes
- do not apply to wounds or damaged skin

Stop use and ask a doctor if

symptoms persist for more than 7 days or clear up and occur again within a few days

- redness is present
- irritation develops
- condition worsens

PREGNANCY OR BREAST FEEDING

If pregnant or breast-feeding, ask a healthcare professional before use.

Keep out of reach of children. If swallowed, seek immediate medical help or contact a Poison Control Center right away. (1-800-222-1222)

Directions

Adults and children over 12 years:

- apply generously to affected area
- massage into painful area until thoroughly absorbed
- repeat if necessary, but not more than 4 times daily

Other Information

Store at 20-25°C (68-77°F)

Inactive Ingredients

Alpha-lipoic acid, Caprylyl Glycol, Cetylalcohol, Coco Caprylate/Caprate, Curcuma longa, Dimethicone, DMDM Hydantoin, Ethylhexylglycerin, Glycerin, Glyceryl Stearate, Hexylene Glycol, Ocimum sanc, Octyl Methoxycinnamate, Olibanum, PEG-100 Stearate, Petrolatum, Phenoxyethanol, Rosmarinus, Salix Alba, Stearic Acid, Stearyl Stearate, Tocopheryl Acetate (Vitamin-E), Water, Zingiber

Questions?

Call 877-669-4227

PRINCIPAL DISPLAY PANEL - 100 mL Tube Label

Odorless • Non-greasy
Fast-acting

Tru-micin®

Topical Analgesic

Temporary relief of pain
associated with
joint, muscle inflammation
and nerve damage

3.5 fl. oz (100 ml)

NDC 51230-418-01